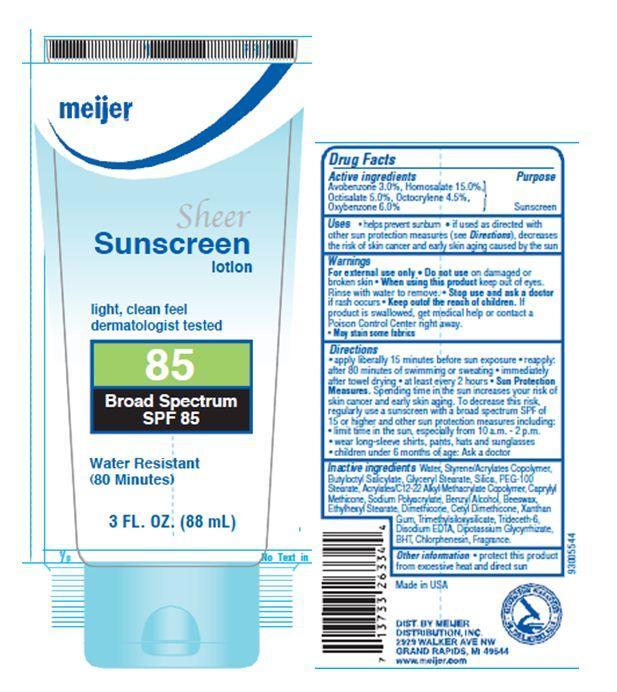 DRUG LABEL: MEIJER
NDC: 41250-035 | Form: LOTION
Manufacturer: Meijer Distribution Inc 
Category: otc | Type: HUMAN OTC DRUG LABEL
Date: 20130712

ACTIVE INGREDIENTS: AVOBENZONE 3 g/100 g; HOMOSALATE 15 g/100 g; OCTISALATE 5 g/100 g; OCTOCRYLENE 4.5 g/100 g; OXYBENZONE 6 g/100 g
INACTIVE INGREDIENTS: WATER; GLYCERYL MONOSTEARATE; SILICON DIOXIDE; PEG-100 STEARATE; CAPRYLYL TRISILOXANE; BENZYL ALCOHOL; YELLOW WAX; ETHYLHEXYL STEARATE; DIMETHICONE; XANTHAN GUM; TRIDECETH-6; EDETATE DISODIUM; GLYCYRRHIZINATE DIPOTASSIUM; BUTYLATED HYDROXYTOLUENE; CHLORPHENESIN

Drug Facts

Active ingredients
Avobenzone 3.0%

Homosalate 15.0%

Octisalate 5.0%

Octocrylene 4.5%

Oxybenzone 6.0%

Purpose

Sunscreen

Uses

- helps prevent sunburn
- if used as directed with other sun protection measures(see Directions), decreases the risk of skin cancer and early skin aging caused by the sun

Warnings

For external use only

Do not use

on damaged or broken skin

When using this product

keep out of eyes. Rinse with water to remove.

Stop use and ask a doctor

if rash occurs

Keep out of reach of children. If product is swallowed, get medical help or contact a Poison Control Center right away.

PRECAUTIONS

- May stain some fabrics

Directions

- apply liberally 15 minutes before sun exposure
- reapply after 80 minutes of swimming or sweating
- immediately after towel drying
- at least every 2 hours
- Sun Protection Measures
- Spending time in the sun increases your risk of skin cancer and early skin aging. To decrease this risk, regularly use a sunscreen with a broad spectrum SPF of 15 or higher and other sun protection measures including:

- limit time in the sun, especially from 10 a.m.-2 p.m.
- wear long sleeve shirts, pants, hats and sunglasses
- children under 6 months of age: Ask a doctor.

Inactive ingredients

Water, Styrene/Acrylates Copolymer, Butyloctyl Salicylate, Glyceryl Stearate, Silica, PEG-100 Stearate, Acrylates/C12-22 Alkyl Methacrylate Copolymer, Caprylyl Methicone, Sodium Polyacrylate, Benzyl Alcohol, Beeswax, Ethylhexyl Stearate, Dimethicone, Cetyl Dimethicone, Xanthan Gum, Trimethylsiloxysilicate, Trideceth-6, Disodium EDTA, Dipotassium Glycyrrhizate, BHT, Chlorphenesin, Fragrance..

Principal Display Panel

meijer

Sheer

Sunscreen lotion

light, clean feel

dermatologist tested

85

Broad Spectrum 85

Water Resistant

(80 Minutes)

3 FL. OZ.

(88 mL)

Other information

- protect the product from excessive heat and direct sun.